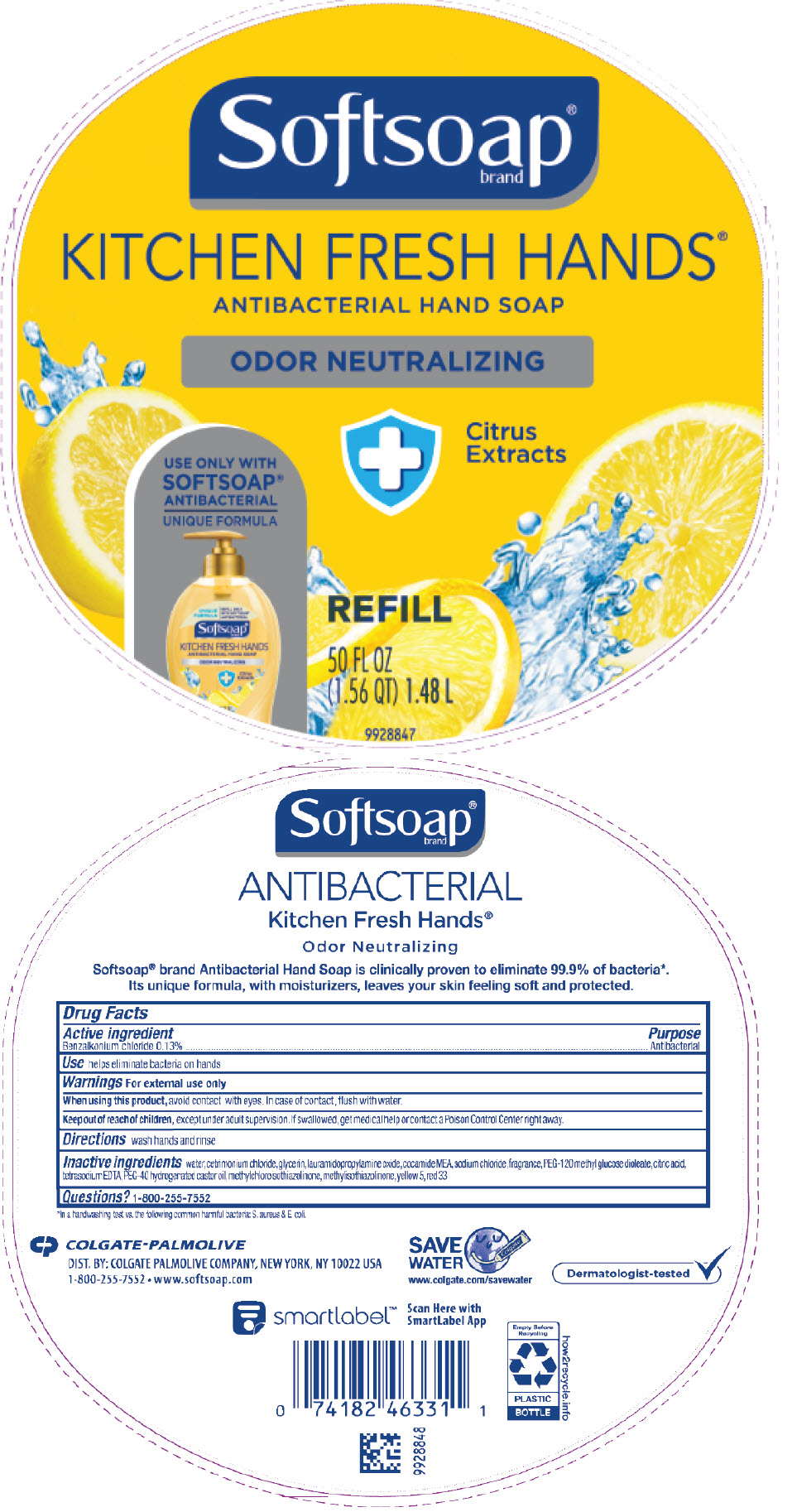 DRUG LABEL: SoftSoap Antibacterial Kitchen Fresh Hands
NDC: 35000-088 | Form: LIQUID
Manufacturer: COLGATE PALMOLIVE COMPANY
Category: otc | Type: HUMAN OTC DRUG LABEL
Date: 20191210

ACTIVE INGREDIENTS: BENZALKONIUM CHLORIDE 1.33 mg/1 mL
INACTIVE INGREDIENTS: WATER; CETRIMONIUM CHLORIDE; GLYCERIN; LAURAMIDOPROPYLAMINE OXIDE; COCO MONOETHANOLAMIDE; SODIUM CHLORIDE; PEG-120 METHYL GLUCOSE DIOLEATE; CITRIC ACID MONOHYDRATE; EDETATE SODIUM; POLYOXYL 40 HYDROGENATED CASTOR OIL; METHYLCHLOROISOTHIAZOLINONE; METHYLISOTHIAZOLINONE; FD&C YELLOW NO. 5; D&C RED NO. 33

SoftSoap® Antibacterial Hand Soap Kitchen Fresh Hands®

Drug Facts

Active ingredient

Benzalkonium chloride 0.13%

Purpose

Antibacterial

Use

helps eliminate bacteria on hands

Warnings

For external use only

When using this product, avoid contact with eyes. In case of contact, flush with water.

Keep out of reach of children, except under adult supervision. If swallowed, get medical help or contact a Poison Control Center right away.

Directions

wash hands and rinse

Inactive ingredients

water, cetrimonium chloride, glycerin, lauramidopropylamine oxide, cocamide MEA, sodium chloride, fragrance, PEG-120 methyl glucose dioleate, citric acid, tetrasodium EDTA, PEG-40 hydrogenated castor oil, methylchloroisothiazolinone, methylisothiazolinone, yellow 5, red 33

Questions?

1-800-255-7552

DIST. BY: COLGATE PALMOLIVE COMPANY, NEW YORK, NY 10022 USA

PRINCIPAL DISPLAY PANEL - 1.48 L Bottle Label

Softsoap®
brand

KITCHEN FRESH HANDS®
ANTIBACTERIAL HAND SOAP

ODOR NEUTRALIZING

Citrus
Extracts

USE ONLY WITH
SOFTSOAP®
ANTIBACTERIAL
UNIQUE FORMULA

REFILL

50 FL OZ
(1.56 QT) 1.48 L

9928847